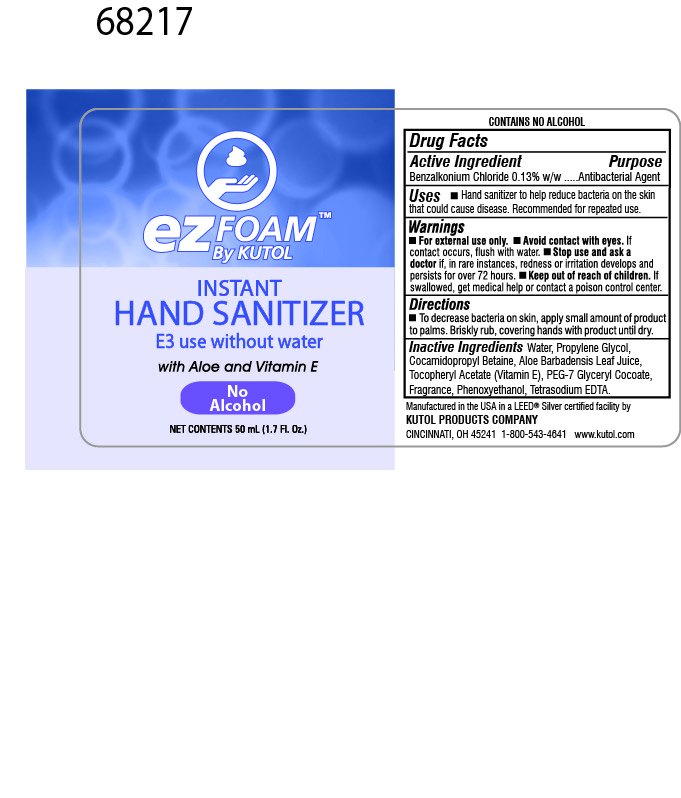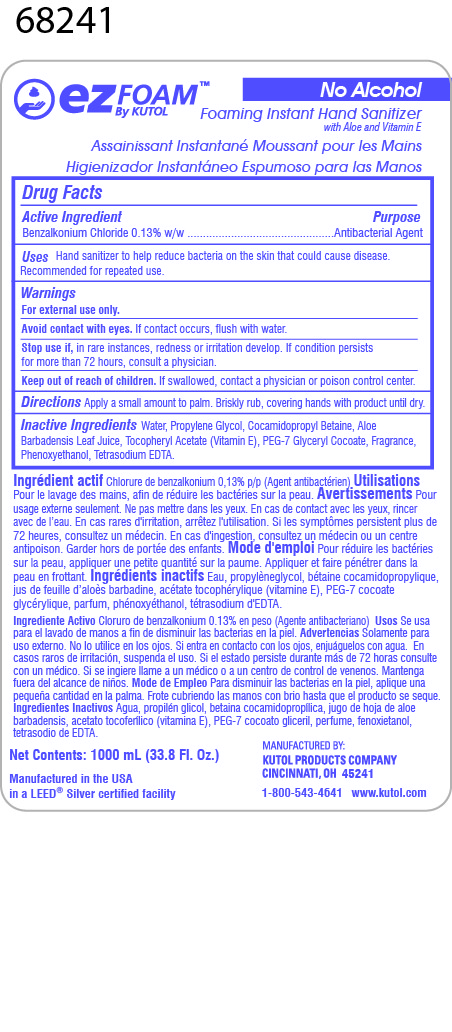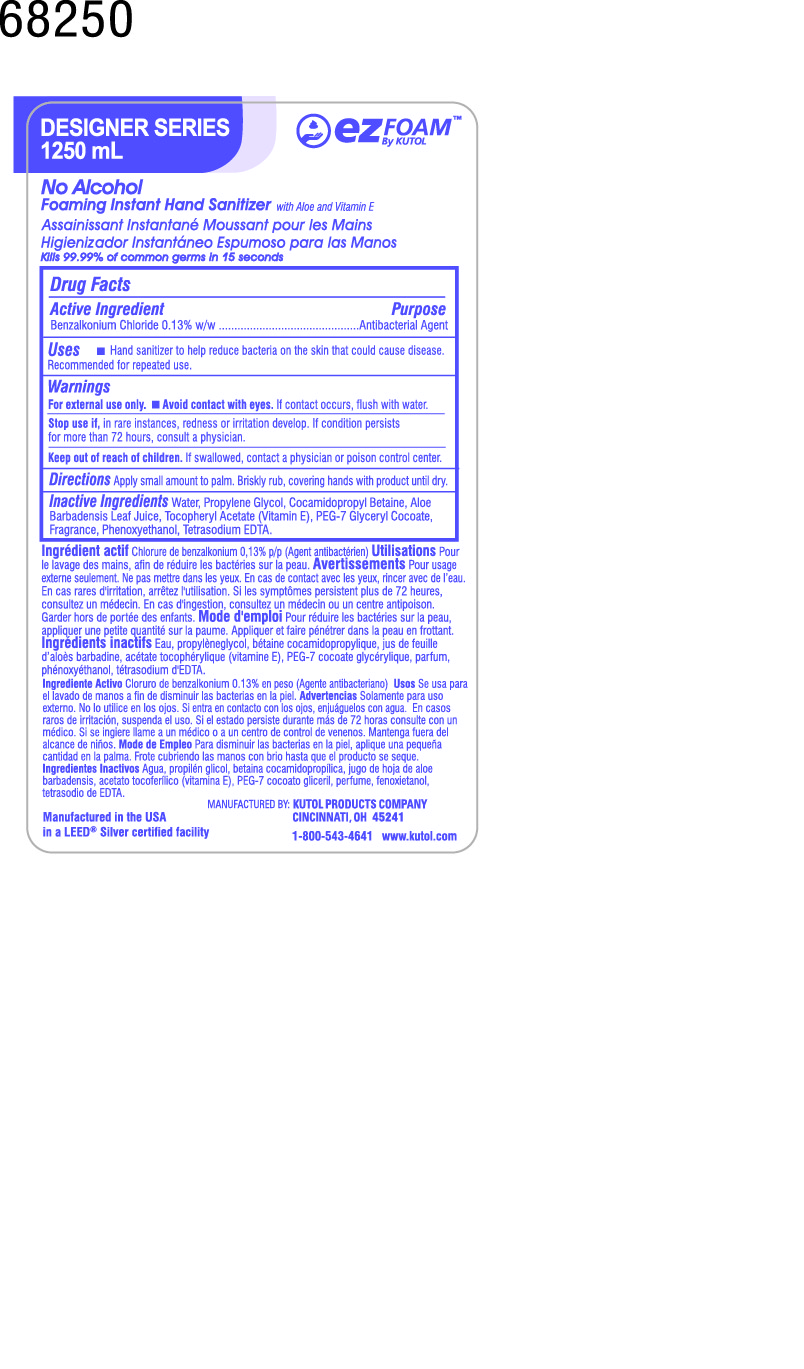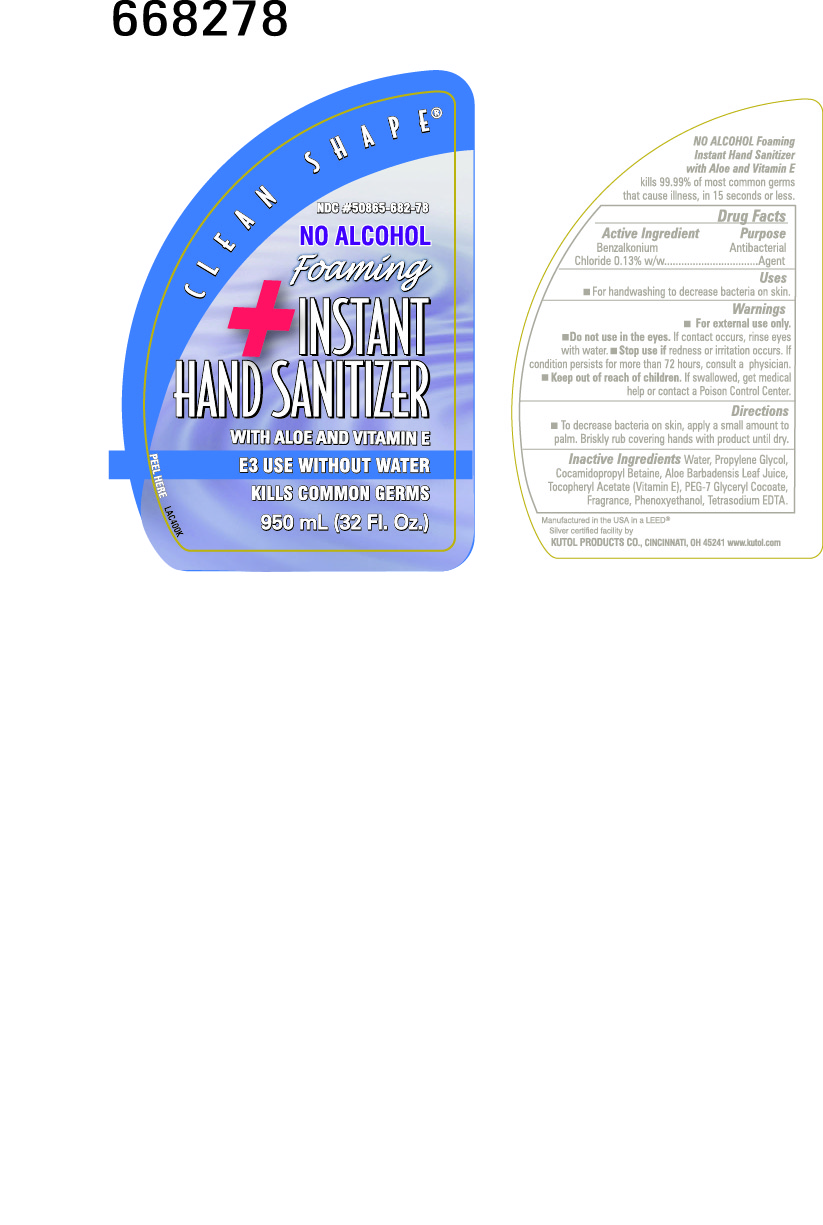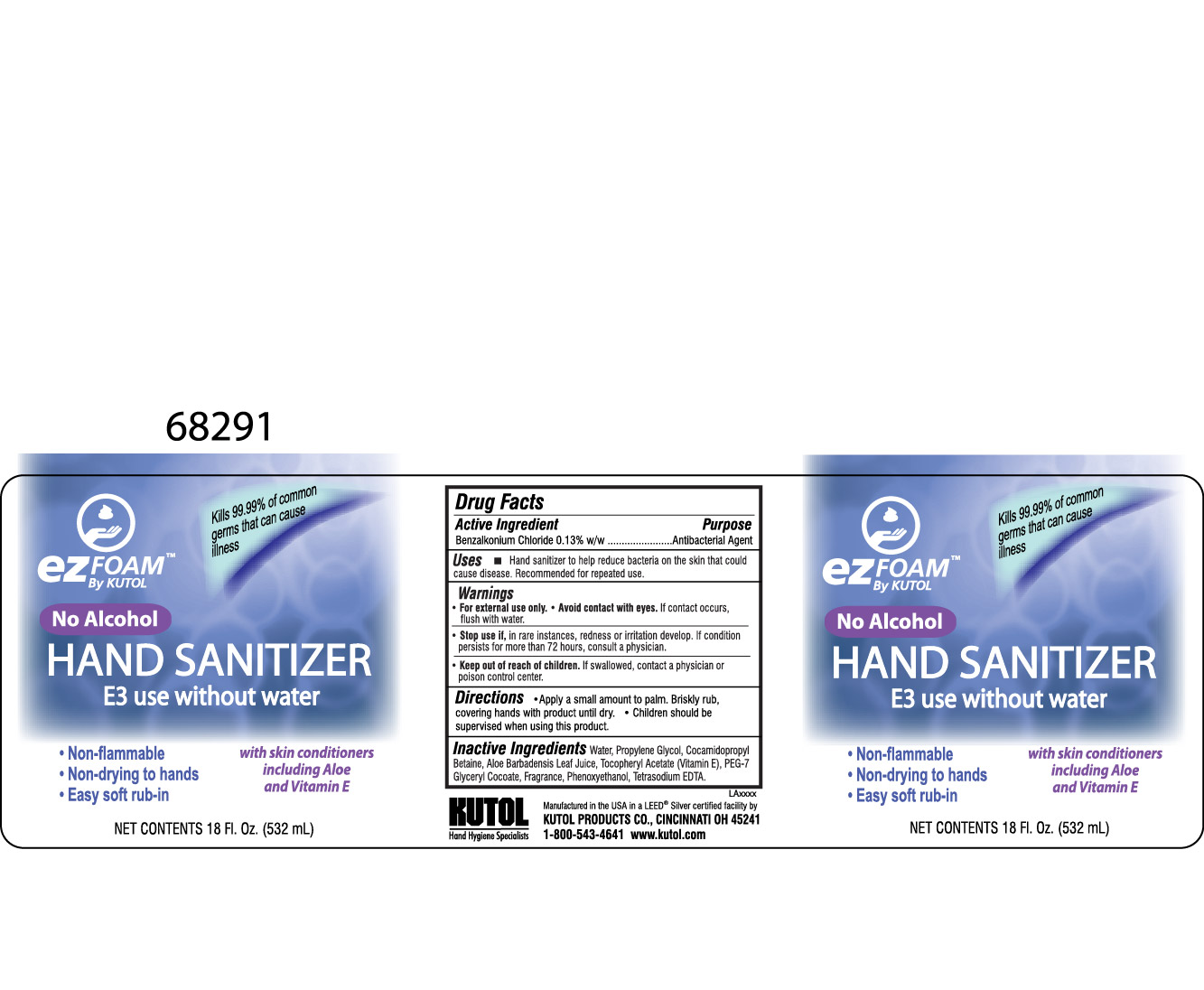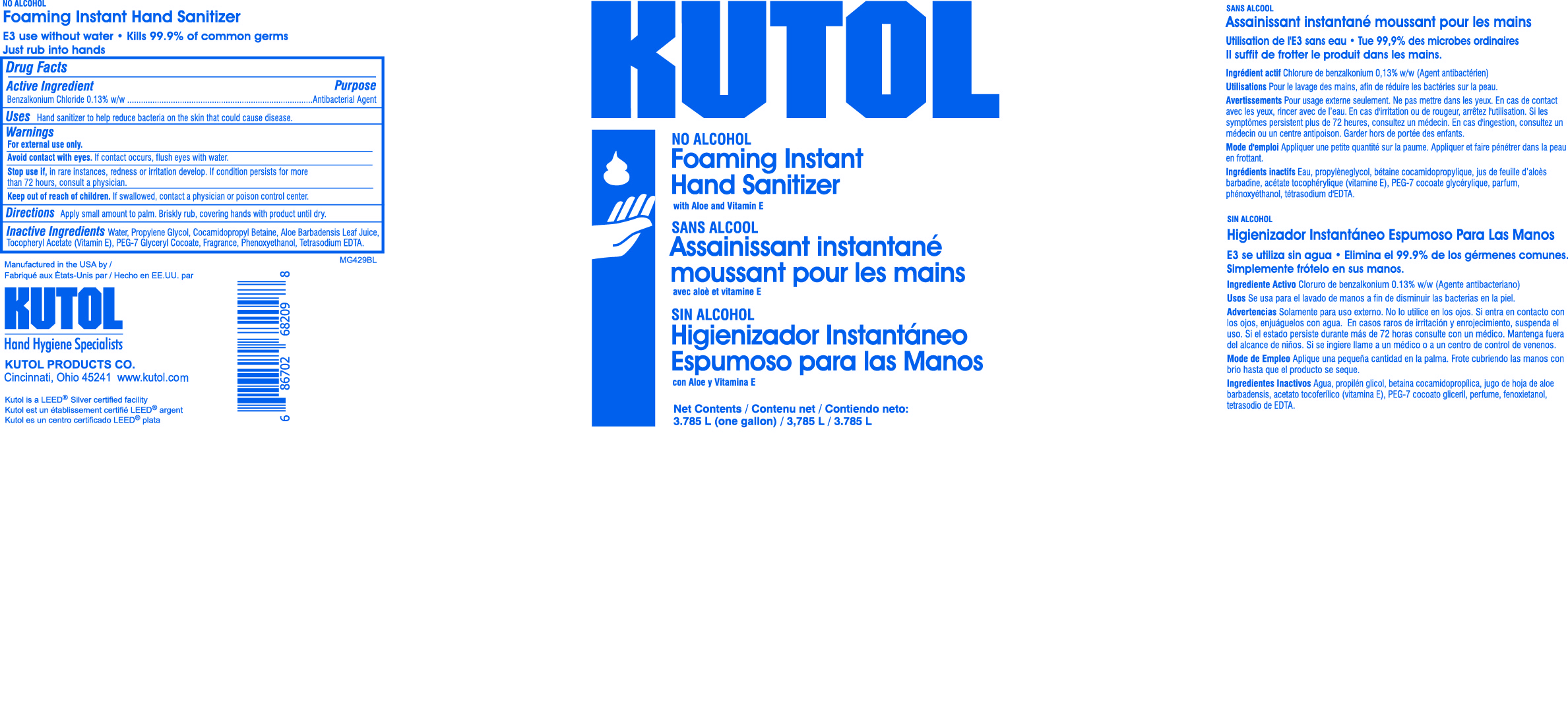 DRUG LABEL: Foaming Instant Hand Sanitizer with Aloe and Vitamin E
NDC: 50865-207 | Form: SOLUTION
Manufacturer: Kutol Products Company, Inc.
Category: otc | Type: HUMAN OTC DRUG LABEL
Date: 20190116

ACTIVE INGREDIENTS: BENZALKONIUM CHLORIDE 0.13 g/100 mL
INACTIVE INGREDIENTS: WATER; EDETATE SODIUM; COCAMIDOPROPYL BETAINE; PEG-7 GLYCERYL COCOATE; PROPYLENE GLYCOL; PHENOXYETHANOL; ALOE VERA LEAF; .ALPHA.-TOCOPHEROL ACETATE, DL-

Foaming Instant Hand Sanitizer with Aloe and Vitamin E

ACTIVE INGREDIENT

Benzalkonium Chloride 0.13% w/w.....Antibacterial Agent

INACTIVE INGREDIENT

Water, Fragrance, Aloe Barbadensis Leaf, Tocopheryl Acetate, Cocamidopropyl Betaine, Propylene Glycol, Phenoxyethanol, PEG-7 Glyceryl Cocoate, Tetrasodium EDTA.

PURPOSE

Hand sanitizer to help reduce bacteria on the skin that could cause disease. Recommended for repeated use.

WARNINGS

For external use only.

Avoid contact with eyes. If contact occurs, flush with water.

Stop use if, in rare instances, redness or irritation develop. If condition persists for more than 72 hours, consult a physician.

Keep out of reach of children. If swallowed, contact a physician or poison control center.

DOSAGE AND ADMINISTRATION

To decrease bacteria on skin, apply small amount to palm. Briskly rub, covering hands with product until dry.

INDICATIONS AND USAGE

Hand sanitizer to help reduce bacteria on the skin that could cause disease. Recommended for repeated use.

Avoid contact with eyes. If contact occurs, flush with water.

Stop use if, in rare instances, redness or irritation develop. If condition persists for more than 72 hours, consult a physician.

Keep out of reach of children. If swallowed, contact a physician or poison control center.

Keep out of reach of children. If swallowed, contact a physician or poison control center.